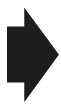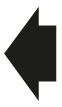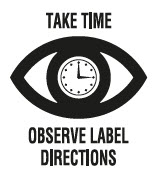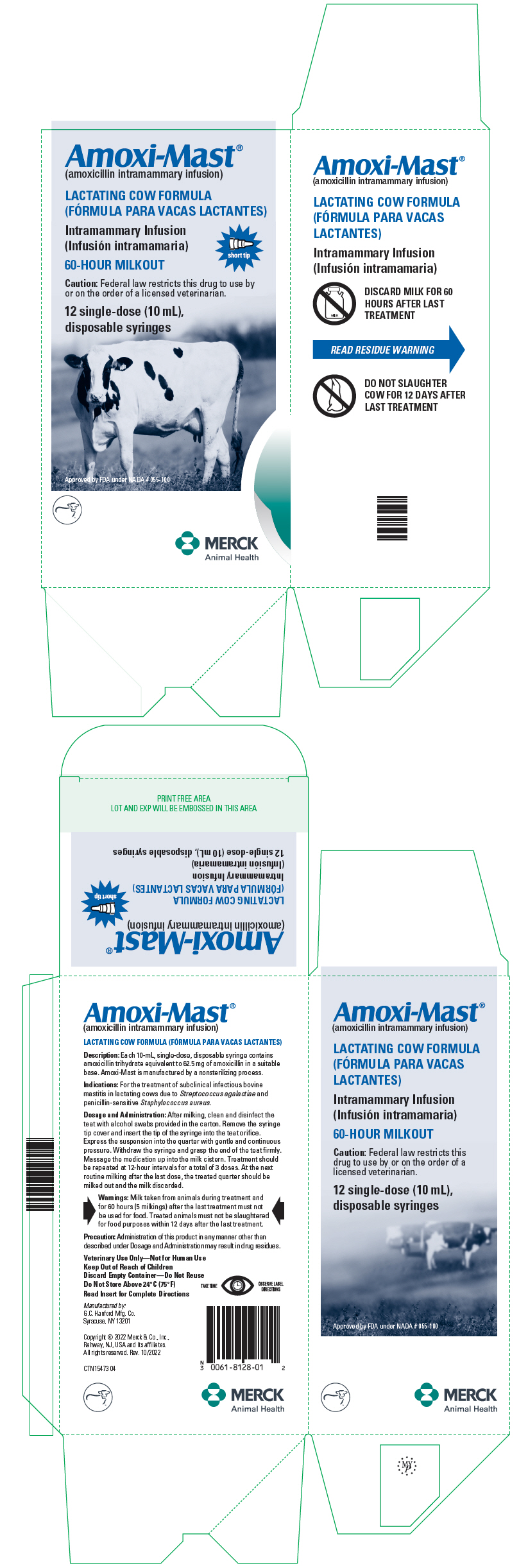 DRUG LABEL: Amoxi-Mast
NDC: 0061-8128 | Form: SUSPENSION
Manufacturer: Merck Sharp & Dohme Corp.
Category: animal | Type: PRESCRIPTION ANIMAL DRUG LABEL
Date: 20241113

ACTIVE INGREDIENTS: AMOXICILLIN 62.5 mg/10 mL

Amoxi-Mast®
(amoxicillin intramammary infusion)

LACTATING COW FORMULA
(FÓRMULA PARA VACAS LACTANTES)

Intramammary Infusion
(Infusión intramamaria)

CAUTION: Federal law restricts this drug to use by or on the order of a licensed veterinarian.

Amoxi-Mast (amoxicillin intramammary infusion) is specially prepared for the treatment of bovine mastitis in lactating cows.

DESCRIPTION

DESCRIPTION: Amoxi-Mast is a stable, nonirritating suspension of amoxicillin trihydrate containing the equivalent of 62.5 mg of amoxicillin per disposable syringe. Amoxi-Mast is manufactured by a nonsterilizing process.

Amoxicillin trihydrate is a semisynthetic penicillin derived from the penicillin nucleus, 6-amino-penicillanic acid. Chemically, it is d(-)-α-amino-p-hydroxybenzyl penicillin trihydrate.

MECHANISM OF ACTION

ACTION: Amoxicillin trihydrate is bactericidal in action against susceptible organisms. It is a broad-spectrum antibiotic which is effective against common infectious mastitis pathogens, namely Streptococcus agalactiae and penicillin-sensitive Staphylococcus aureus.

In vitro studies have demonstrated the susceptibility of the following strains of bacteria: α- and β-haemolytic streptococci, nonpenicillinase-producing staphylococci, and Escherichia coli. Susceptibility has not been demonstrated against penicillinase-producing bacteria, particularly resistant staphylococci. Most strains of Pseudomonas, Klebsiella, and Enterobacter are resistant. The clinical or subclinical significance of these in vitro studies is not known.

INDICATIONS AND USAGE

INDICATIONS: Amoxi-Mast is indicated in the treatment of subclinical infectious bovine mastitis in lactating cows due to Streptococcus agalactiae and penicillin-sensitive Staphylococcus aureus. Early detection and treatment of mastitis is advised.

WARNINGS

WARNINGS: Milk taken from animals during treatment and for 60 hours (5 milkings) after the last treatment must not be used for food. Treated animals must not be slaughtered for food purposes within 12 days after the last treatment.

PRECAUTIONS

PRECAUTION: Because it is a derivative of 6-amino-penicillanic acid, Amoxi-Mast has the potential for producing allergic reactions. Such reactions are rare; however, should they occur, the subject should be treated with the usual agents (antihistamines, pressor amines).

DOSAGE AND ADMINISTRATION: Milk out udder completely. Wash udder and teats thoroughly with warm water containing a suitable dairy antiseptic. Dry thoroughly. Clean and disinfect the teat with alcohol swabs provided in the carton. Remove the syringe tip cover and insert the tip of the syringe into the teat orifice. Express the suspension into the quarter with gentle and continuous pressure. Withdraw the syringe and grasp the end of the teat firmly. Massage the medication up into the milk cistern.

For optimum response, the drug should be administered by intramammary infusion in each infected quarter as described above. Treatment should be repeated at 12-hour intervals for a total of 3 doses. At the next routine milking after the last dose, the treated quarter should be milked out and the milk discarded.

Each carton contains 12 alcohol swabs to facilitate proper cleaning and disinfecting of the teat orifice.

HOW SUPPLIED

HOW SUPPLIED: Amoxi-Mast is supplied in cartons of 12 single-dose syringes with 12 alcohol swabs. Each 10-mL, disposable syringe contains amoxicillin trihydrate equivalent to 62.5 mg of amoxicillin activity.

STORAGE AND HANDLING

Do Not Store Above 24°C (75°F)

Approved by FDA under NADA # 055-100

Manufactured by:
G.C. Hanford Mfg. Co.
Syracuse, NY 13201

Copyright © 2022 Merck & Co., Inc.,
Rahway, NJ, USA and its affiliates.
All rights reserved.

Rev 10/2022

INS15427 04

PRINCIPAL DISPLAY PANEL - 10 mL Syringe Carton

Amoxi-Mast®
(amoxicillin intramammary infusion)

LACTATING COW FORMULA

Intramammary Infusion

short tip

60-HOUR MILKOUT

Caution: Federal law restricts this drug to use by
or on the order of a licensed veterinarian.

12 single-dose (10 mL),
disposable syringes

Approved by FDA under NADA # 055-100

MERCK
Animal Health